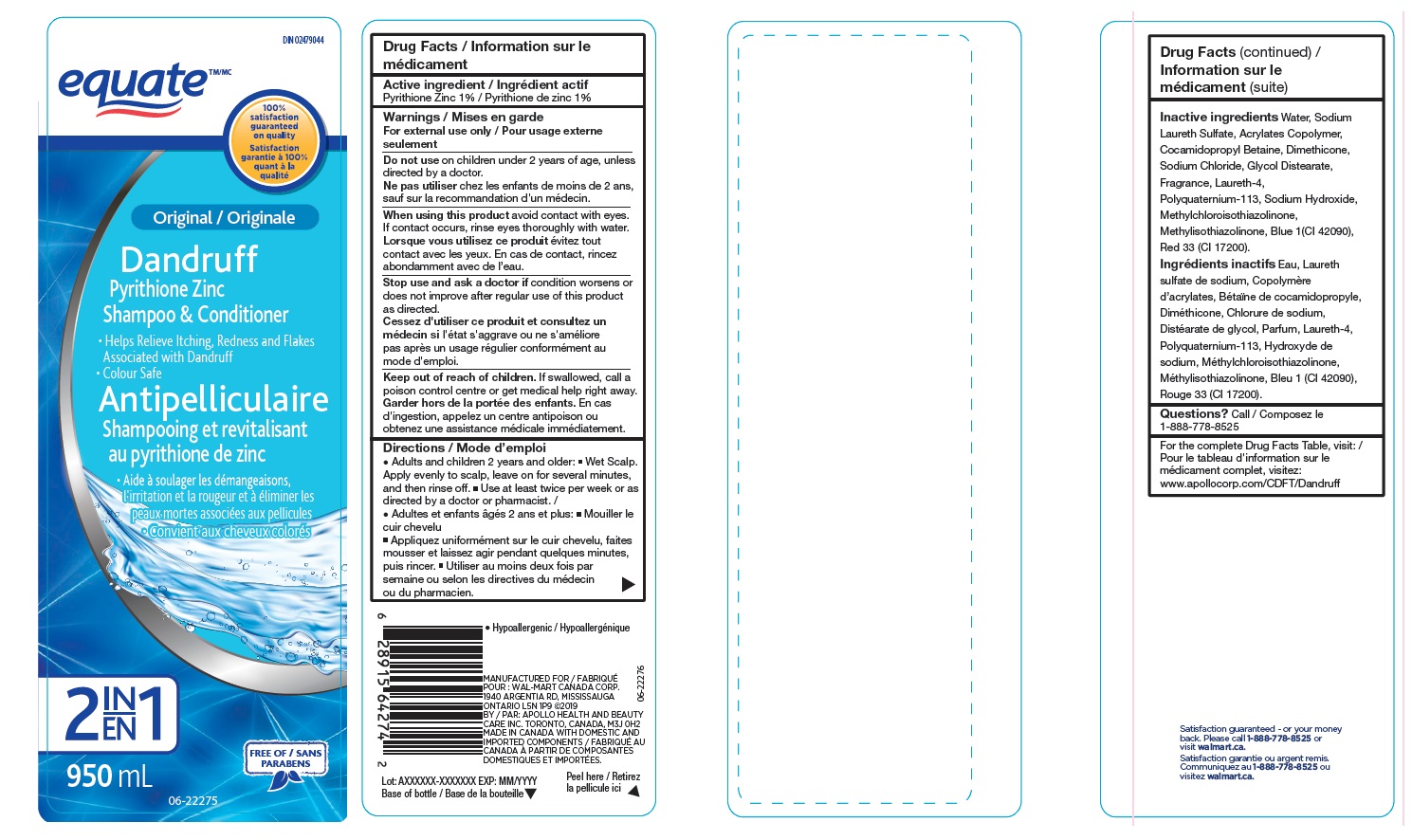 DRUG LABEL: Walmart
NDC: 79903-897 | Form: LOTION/SHAMPOO
Manufacturer: Wal-Mart Stores, Inc
Category: otc | Type: HUMAN OTC DRUG LABEL
Date: 20241020

ACTIVE INGREDIENTS: PYRITHIONE ZINC 10 mg/1 mL
INACTIVE INGREDIENTS: WATER; METHACRYLIC ACID - METHYL METHACRYLATE COPOLYMER (1:1); COCAMIDOPROPYL BETAINE; DIMETHICONE; FRAGRANCE CLEAN ORC0600327; LAURETH-4; SODIUM LAURETH SULFATE; ACID RED 337 FREE ACID; DIRECT BLUE 1; POLYQUATERNIUM-11 (1000000 MW); GLYCOL DISTEARATE; SODIUM CHLORIDE; SODIUM HYDROXIDE; METHYLCHLOROISOTHIAZOLINONE/METHYLISOTHIAZOLINONE MIXTURE

Equate Original Shampoo- 79903-897-95

ACTIVE INGREDIENT

Pyrithione Zinc

PURPOSE

For the relief of itching, redness and flaking associated with dandruff

WARNINGS

For External use

DO NOT USE

on children under 2 years of age, unless directed by a doctor.

Stop use and ask a doctor ifcondition worsens or does not improve after regular use of this product
as directed.

WHEN USING

avoid contact with eyes.
If contact occurs, rinse eyes thoroughly with water.

KEEP OUT OF REACH OF CHILDREN

If swallowed, call a poison control centre or get medical help right away.

DOSAGE AND ADMINISTRATION

• Adults and children 2 years and older.

- Wet Scalp. Apply evenly to scalp, leave on for several minutes, and then rinse off. Use at least twice per week or as

directed by a doctor or pharmacist.

INDICATIONS AND USAGE

Relieves itching , redness and flakes associated with Dandruff.

INACTIVE INGREDIENT

Water, Sodium Laureth Sulfate, Acrylates Copolymer, Cocamidopropyl Betaine, Dimethicone,
Sodium Chloride, Glycol Distearate, Fragrance, Laureth-4, Polyquaternium-113, Sodium Hydroxide,
Methylchloroisothiazolinone, Methylisothiazolinone, Blue 1(CI 42090), Red 33 (CI 17200).

STORAGE AND HANDLING

Store at room temperature